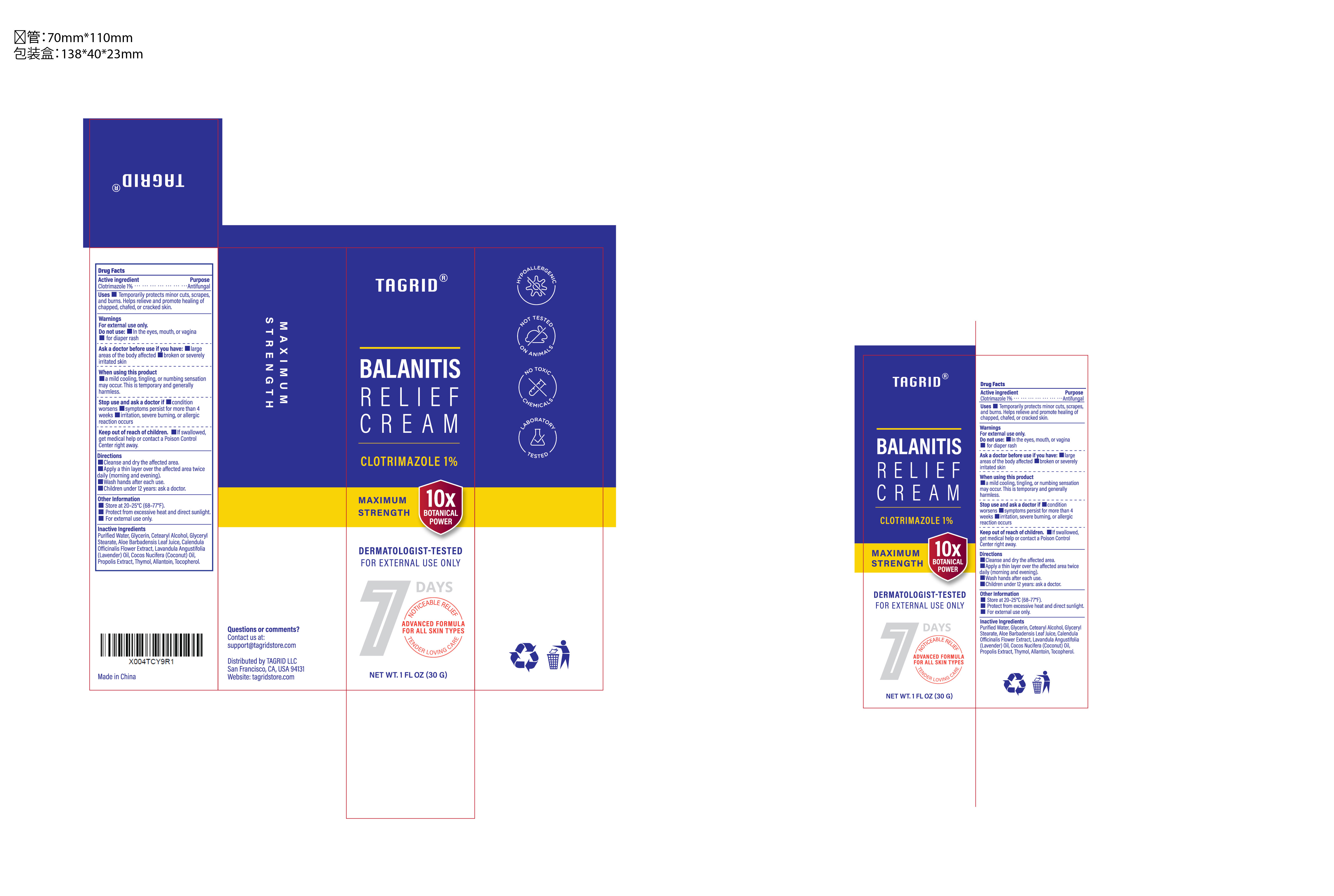 DRUG LABEL: Tagrid Balanitis Relief
NDC: 85384-0018 | Form: CREAM
Manufacturer: TAGRID LLC
Category: otc | Type: HUMAN OTC DRUG LABEL
Date: 20251114

ACTIVE INGREDIENTS: CLOTRIMAZOLE 1 g/100 g
INACTIVE INGREDIENTS: WATER; GLYCERIN; CETOSTEARYL ALCOHOL; GLYCERYL MONOSTEARATE; ALOE VERA LEAF JUICE; CALENDULA OFFICINALIS FLOWER; LAVENDER OIL; COCONUT OIL; PROPOLIS WAX; THYMOL; ALLANTOIN; TOCOPHEROL

Active ingredient:

1. Clotrimazole 1%

PURPOSE

1. Antifungal

Uses:

1. Temporarily protects minor cuts, scrapes, and burns.
2. Helps relieve and promote healing of chapped, chafed, or cracked skin.

WARNINGS

For external use only.

Do not use:

- In the eyes, mouth, or vagina
- for diaper rash

When using this product

- a mild cooling, tingling, or numbing sensation may occur. This is temporary and generally harmless.

Stop use and ask a doctor if

- condition worsens
- symptoms persist for more than 4 weeks
- irritation, severe burning, or allergic reaction occurs

Keep out of reach of children.

If swallowed, get medical help or contact a Poison Control Center right away.

Directions

- Cleanse and dry the affected area.
- Apply a thin layer over the affected area twice daily (morning and evening).
- Wash hands after each use.
- Children under 12 years: ask a doctor.

Inactive Ingredients

- Purified Water
- Glycerin
- Cetearyl Alcohol
- Glyceryl Stearate
- Aloe Barbadensis Leaf Juice
- Calendula Officinalis Flower Extract
- Lavandula Angustifolia (Lavender) Oil
- Cocos Nucifera (Coconut) Oil
- Propolis Extract
- Thymol
- Allantoin
- Tocopherol

Questions or comments?

Contact us at support@tagridstore.com